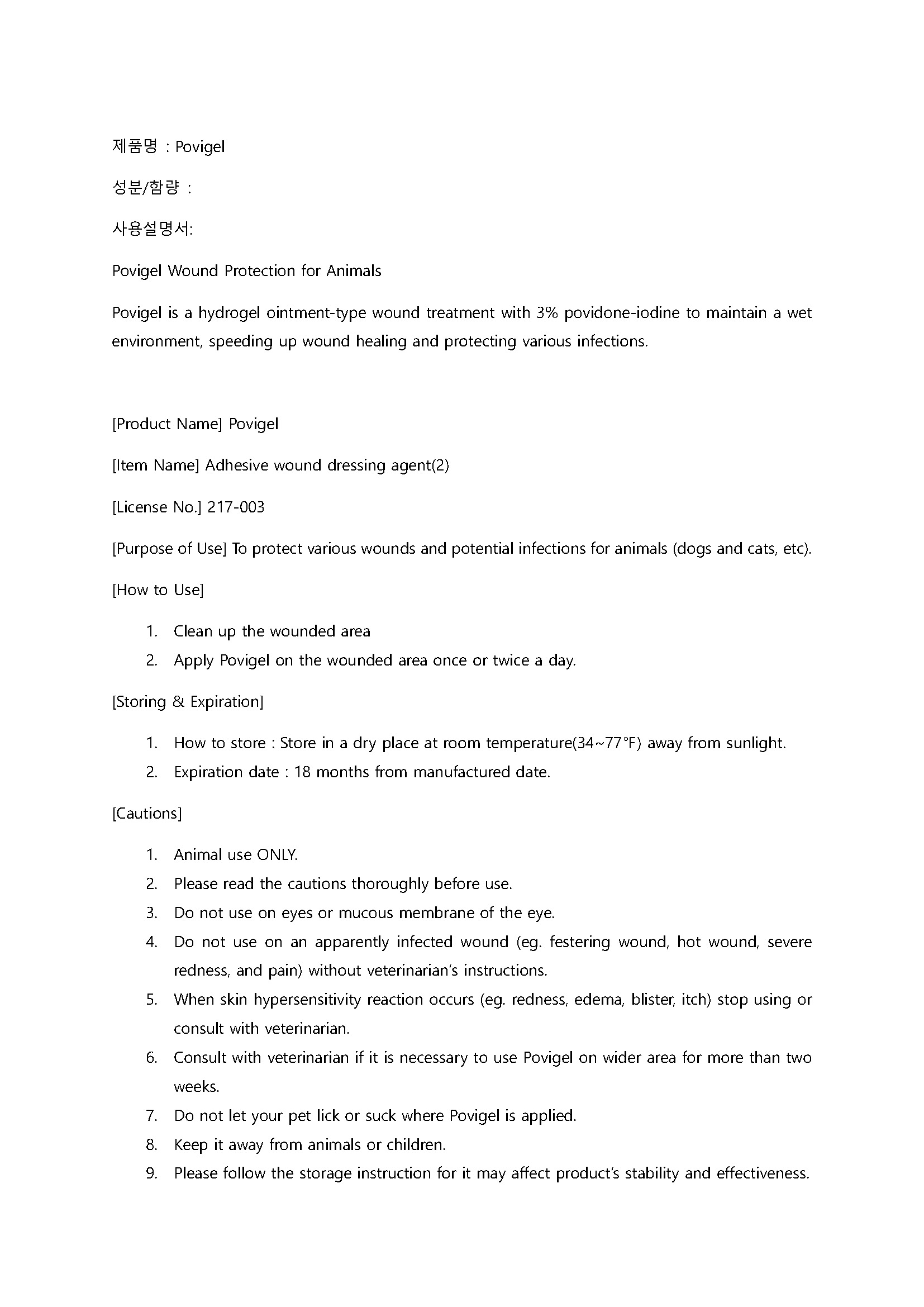 DRUG LABEL: Povigel
NDC: 86200-0001 | Form: GEL
Manufacturer: ELT SCIENCE CORP
Category: animal | Type: OTC ANIMAL DRUG LABEL
Date: 20240325

ACTIVE INGREDIENTS: POVIDONE-IODINE 3 g/100 g
INACTIVE INGREDIENTS: WATER; carbomer 940

ACTIVE INGREDIENT

Povidone Iodine

INACTIVE INGREDIENT

Carbomer 940, Hydrogenated Lecithin,Potassium Iodide, Sodium Hydroxide, Anhydrous Citric Acid, Sodium Phosphate Dibasic Anhydrous, Purified Water

PURPOSE

To protect various wounds and potential infections for animals (dogs and cats, etc).

Keep out of reach of children

INDICATIONS AND USAGE

[How to Use]
1. Clean up the wounded area
2. Apply Povigel on the wounded area once or twice a day.

WARNINGS

[Storing & Expiration]
1. How to store : Store in a dry place at room temperature(34~77℉) away from sunlight.
2. Expiration date : 18 months from manufactured date.

[Cautions]
1. Animal use ONLY.
2. Please read the cautions thoroughly before use.
3. Do not use on eyes or mucous membrane of the eye.
4. Do not use on an apparently infected wound (eg. festering wound, hot wound, severe redness, and pain) without veterinarian’s instructions.
5. When skin hypersensitivity reaction occurs (eg. redness, edema, blister, itch) stop using or consult with veterinarian.
6. Consult with veterinarian if it is necessary to use Povigel on wider area for more than two weeks.
7. Do not let your pet lick or suck where Povigel is applied.
8. Keep it away from animals or children.
9. Please follow the storage instruction for it may affect product’s stability and effectiveness.

DOSAGE AND ADMINISTRATION

For external use only